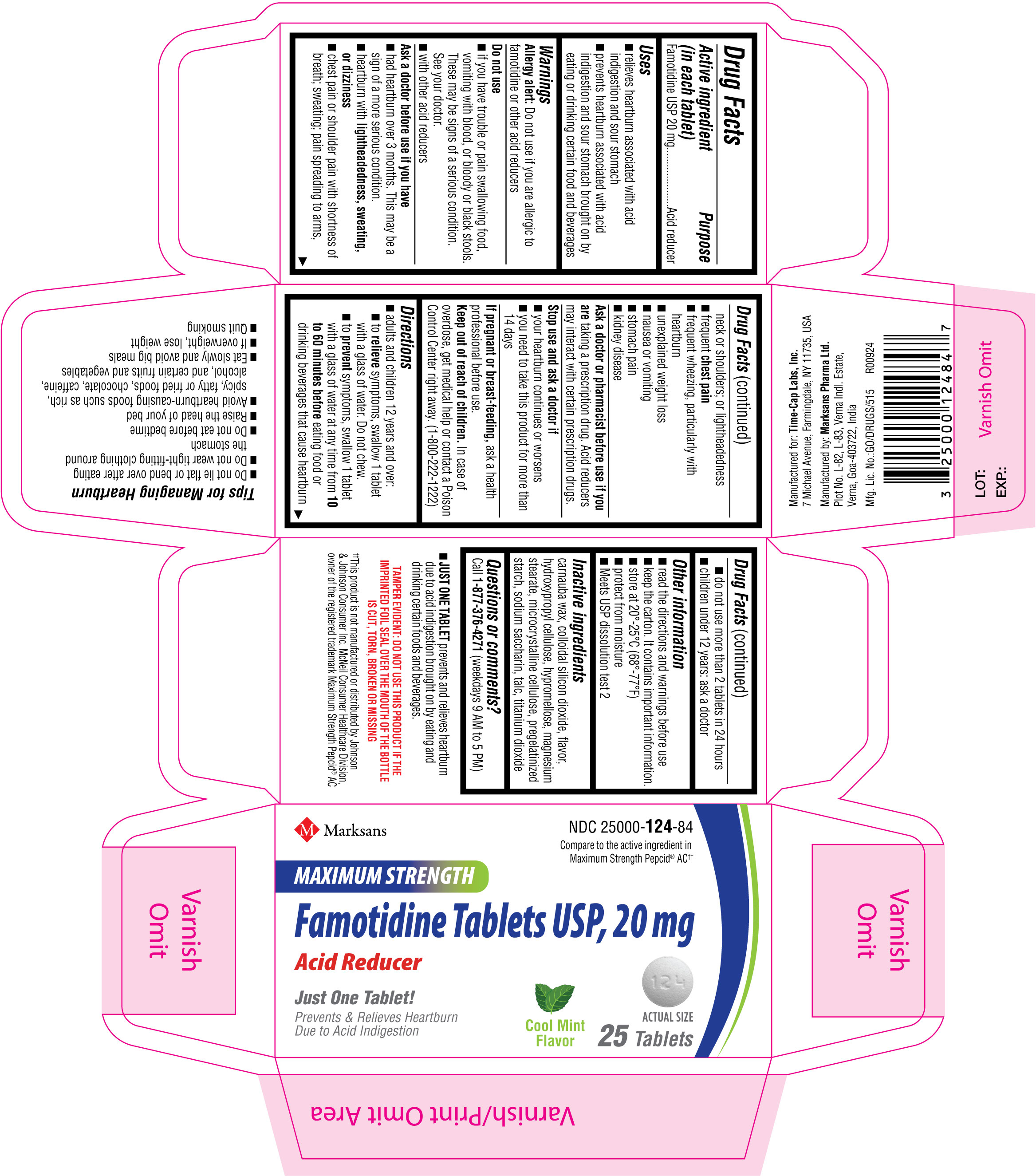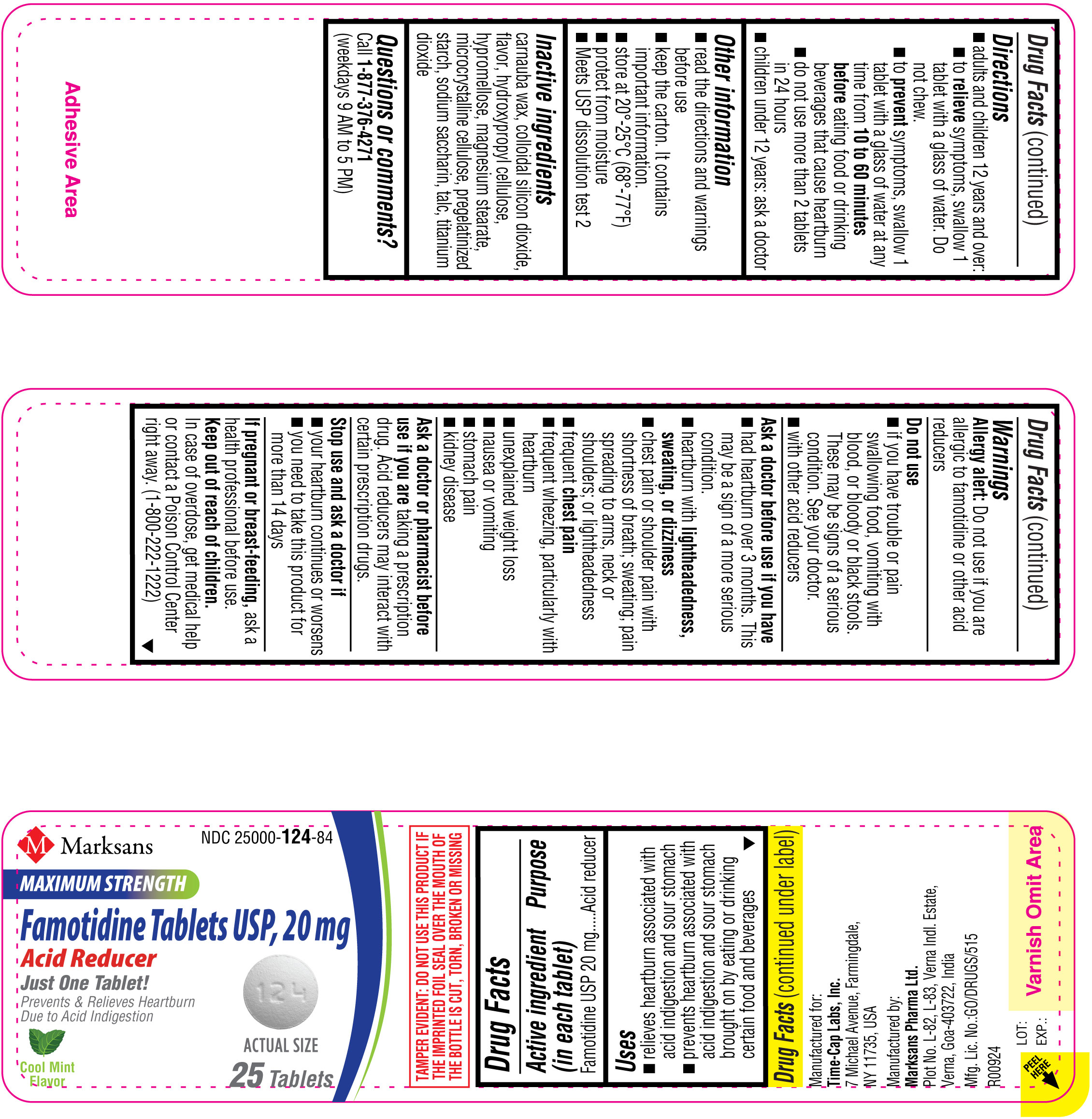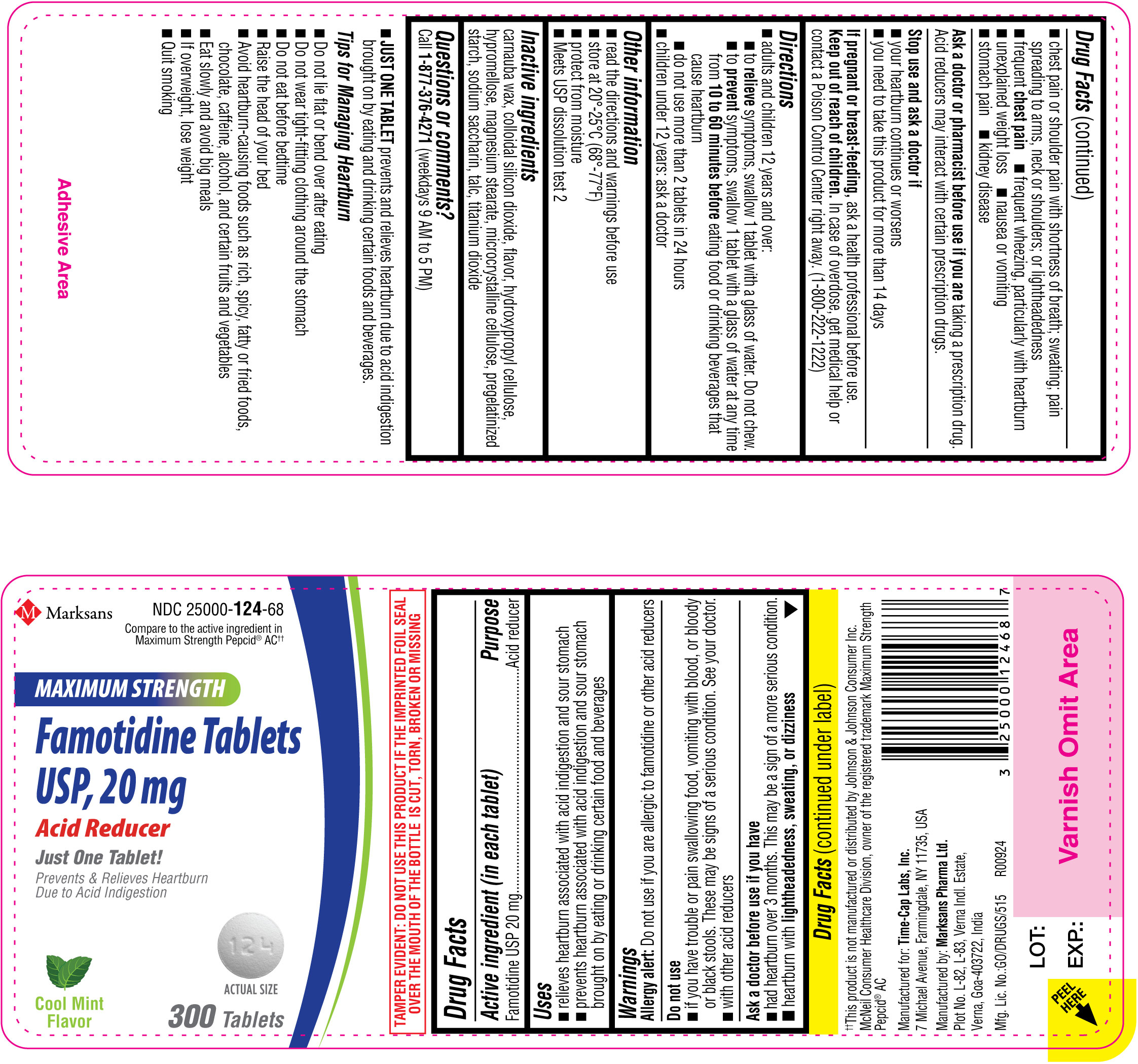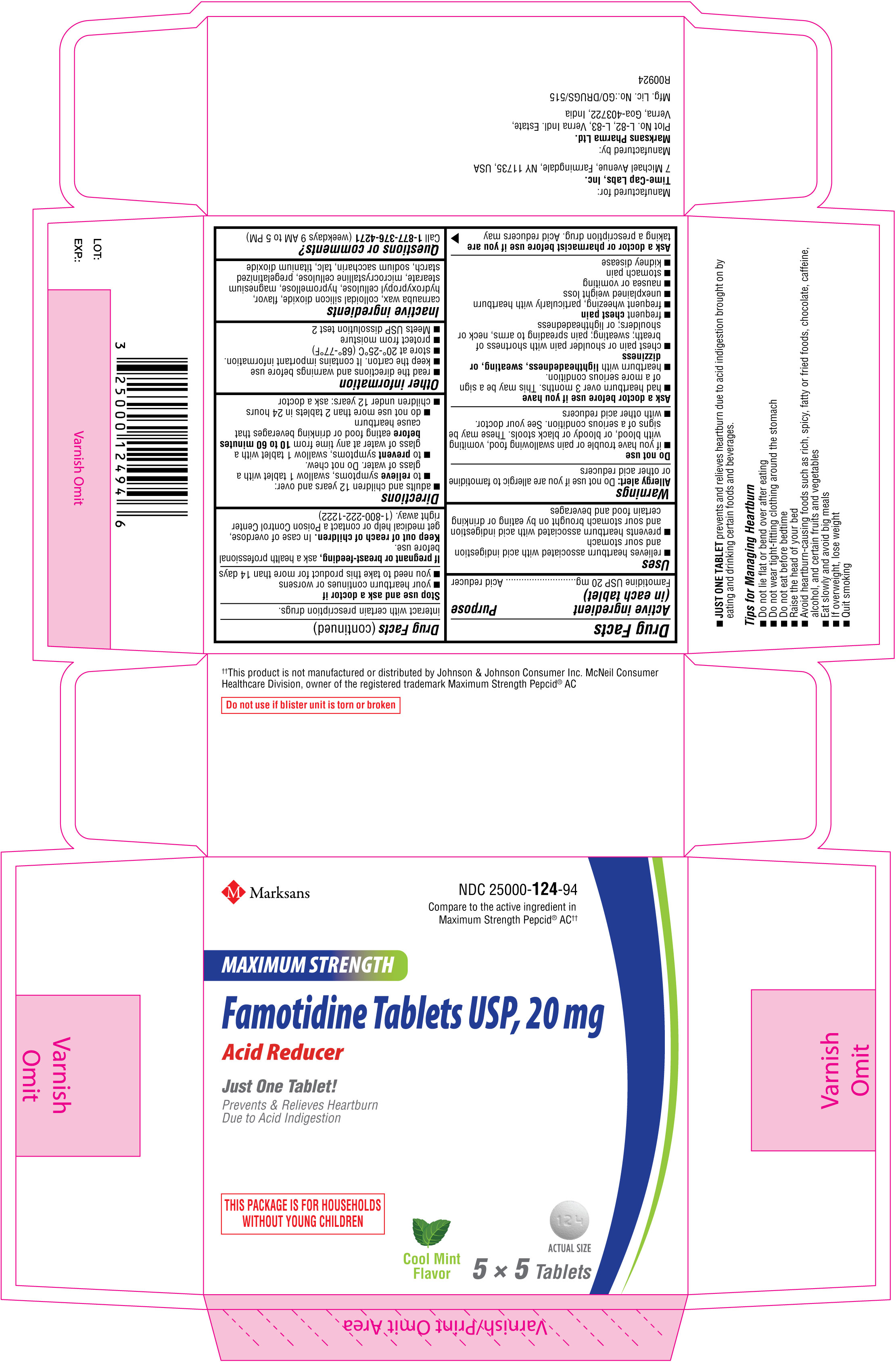 DRUG LABEL: Famotidine 20 mg
NDC: 25000-124 | Form: TABLET, COATED
Manufacturer: MARKSANS PHARMA LIMITED
Category: otc | Type: Human OTC Drug Label
Date: 20250506

ACTIVE INGREDIENTS: FAMOTIDINE 20 mg/1 1
INACTIVE INGREDIENTS: SILICON DIOXIDE; CARNAUBA WAX; HYDROXYPROPYL CELLULOSE, UNSPECIFIED; HYPROMELLOSE, UNSPECIFIED; MAGNESIUM STEARATE; MICROCRYSTALLINE CELLULOSE 102; STARCH, CORN; SACCHARIN SODIUM; TALC; TITANIUM DIOXIDE

Famotidine Tablets USP, 20 mg - Cool Mint Flavor

ACTIVE INGREDIENT(S)

Active ingredient (in each tablet)
Famotidine USP 20 mg

PURPOSE

Acid reducer

USE(S)

Uses
•relieves heartburn associated with acid indigestion and sour stomach
•prevents heartburn associated with acid indigestion and sour stomach brought on by eating or drinking certain food and beverages

WARNINGS

Allergy alert: Do not use if you are allergic to famotidine or other acid reducers

DO NOT USE

•if you have trouble or pain swallowing food, vomiting with blood, or bloody or black stools. These may be signs of a serious condition. See your doctor.
•with other acid reducers

Ask a doctor before use if you have
•had heartburn over 3 months. This may be a sign of a more serious condition.
•heartburn with lightheadedness, sweating, or dizziness
•chest pain or shoulder pain with shortness of breath; sweating; pain spreading to arms, neck or shoulders; or lightheadedness
•frequent chest pain
•frequent wheezing, particularly with heartburn
•unexplained weight loss
•nausea or vomiting
•stomach pain
•kidney disease

Ask a doctor or pharmacist before use if you are taking a prescription drug. Acid reducers may interact with certain prescription drugs.

STOP USE AND ASK DOCTOR IF

Stop use and ask a doctor if
•your heartburn continues or worsens
•you need to take this product for more than 14 days

PREGNANCY/BREASTFEEDING

If pregnant or breast-feeding, ask a health professional before use.

Keep out of reach of children. In case of overdose, get medical help or contact a Poison Control Center right away. (1-800-222-1222)

DIRECTIONS

•adults and children 12 years and over:
- to relieve symptoms, swallow 1 tablet with a glass of water. Do not chew.
- to prevent symptoms, swallow 1 tablet with a glass of water at any time from 10 to 60 minutes before eating food or drinking beverages that cause heartburn
- do not use more than 2 tablets in 24 hours
•children under 12 years: ask a doctor

OTHER INFORMATION

•read the directions and warnings before use
•keep the carton. It contains important information.
•store at 20°-25°C (68°-77°F)
•protect from moisture
•Meets USP dissolution test 2

INACTIVE INGREDIENTS

Inactive ingredients carnauba wax, colloidal silicon dioxide, flavor, hydroxypropyl cellulose, hypromellose, magnesium stearate, microcrystalline cellulose, pregelatinized starch, sodium saccharin, talc, titanium dioxide

Questions or comments? Call 1-877-376-4271 (weekdays 9 AM to 5 PM)

•JUST ONE TABLET prevents and relieves heartburn due to acid indigestion brought on by eating and drinking certain foods and beverages.

Tips for Managing Heartburn
•Do not lie flat or bend over after eating
•Do not wear tight-fitting clothing around the stomach
•Do not eat before bedtime
•Raise the head of your bed
•Avoid heartburn-causing foods such as rich, spicy, fatty or fried foods, chocolate, caffeine, alcohol, and certain fruits and vegetables
•Eat slowly and avoid big meals
•If overweight, lose weight
•Quit smoking

Manufactured for:
Time-Cap Labs, Inc.
7 Michael Avenue,
Farmingdale,
NY 11735, USA

Manufactured by:
Marksans Pharma Ltd.
Plot No. L-82, L-83
Verna Indl. Estate
Verna, Goa-403722, India

PRINCIPAL DISPLAY PANEL

NDC: 25000-124-94
Famotidine Tablets USP 20 mg- Cool mint flavor
25's (5 x 5's blister) count Carton Label

NDC: 25000-124-84
Famotidine Tablets USP 20 mg- Cool mint flavor
25's count Bottle Label

NDC: 25000-124-84
Famotidine Tablets USP 20 mg- Cool mint flavor
25's count Carton Label

NDC: 25000-124-68
Famotidine Tablets USP 20 mg- Cool mint flavor
300's count Bottle Label